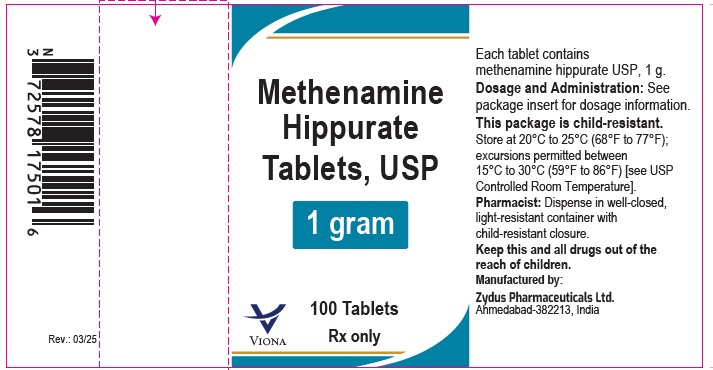 DRUG LABEL: Methenamine hippurate
NDC: 70771-1919 | Form: TABLET
Manufacturer: Zydus Lifesciences Limited
Category: prescription | Type: HUMAN PRESCRIPTION DRUG LABEL
Date: 20250312

ACTIVE INGREDIENTS: METHENAMINE HIPPURATE 1 g/1 1
INACTIVE INGREDIENTS: CROSPOVIDONE, UNSPECIFIED; MAGNESIUM STEARATE; POVIDONE, UNSPECIFIED; SACCHARIN SODIUM; SILICON DIOXIDE

Methenamine Hippurate Tablets, USP

PACKAGE LABEL.PRINCIPAL DISPLAY PANEL

NDC 70771-1919-1

Methenamine Hippurate Tablets, USP 1gram

100 tablets

Rx only